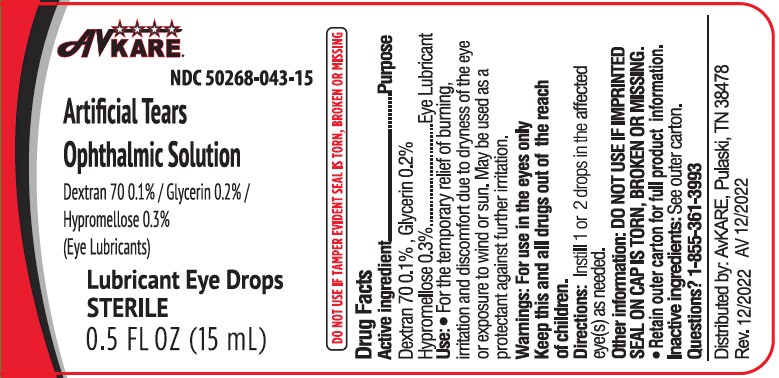 DRUG LABEL: Artificial Tears
NDC: 50268-043 | Form: SOLUTION/ DROPS
Manufacturer: AvPAK
Category: otc | Type: HUMAN OTC DRUG LABEL
Date: 20250421

ACTIVE INGREDIENTS: DEXTRAN 70 1 mg/1 mL; GLYCERIN 2 mg/1 mL; HYPROMELLOSES 3 mg/1 mL
INACTIVE INGREDIENTS: BORIC ACID; CALCIUM CHLORIDE; GLYCINE; MAGNESIUM CHLORIDE; POLYSORBATE 80; POTASSIUM CHLORIDE; WATER; SODIUM CHLORIDE; ZINC CHLORIDE; BENZALKONIUM CHLORIDE

Artificial Tears Ophthalmic Solution

ACTIVE INGREDIENT

Active ingredients | Purpose
Dextran 70 0.1% | Lubricant
Glycerin 0.2% | Lubricant
Hypromellose 0.3% | Lubricant

Uses

- For the temporary relief of burning, irritation and discomfort due to dryness of the eye or exposure to wind or sun
- May be used as a protectant against further irritation

Warnings

For use in the eyes only

Do not use

- if this solution changes color or becomes cloudy

When using this product

- Avoid contamination, do not touch tip of container to any surface
- Replace cap after use

Stop use and ask a doctor if you experience any of the following:

- You experience eye pain, changes in vision, continued redness and irritation of the eye
- The condition worsens or persists for more than 72 hours

Keep out of reach of children.

If swallowed, get medical help or contact a Poison Control Center right away (1-800-222-1222).

Directions

- Shake well before use
- Instill 1 or 2 drops in the affected eye(s) as needed

Other Information

- store at room temperature

Inactive ingredients:

benzalkonium chloride, boric acid, calcium chloride, glycine, hydrochloric acid and/or sodium hydroxide (to adjust pH), magnesium chloride, polysorbate 80, potassium chloride, purified water, sodium chloride, zinc chloride.

Questions?

1-855-361-3993

Distributed by:
AvKARE

Pulaski, TN 38478

www.avkare.com

Rev. 12/2022 AV 12/2022